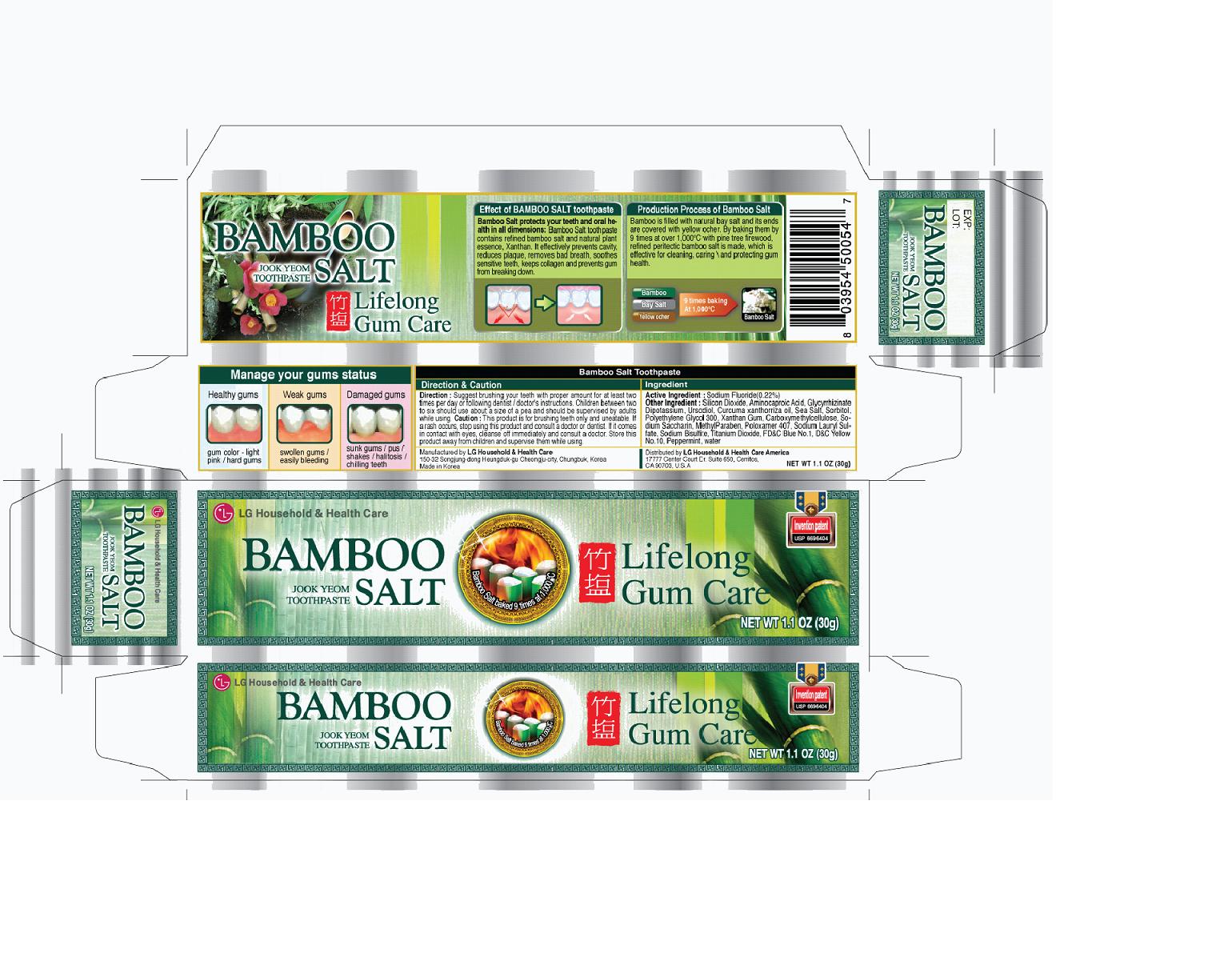 DRUG LABEL: BAMBOO SALT  Eunganggo Jook Yeom
NDC: 53208-505 | Form: PASTE
Manufacturer: LG Household and Healthcare, Inc.
Category: otc | Type: HUMAN OTC DRUG LABEL
Date: 20110316

ACTIVE INGREDIENTS: SILICON DIOXIDE   20 g/100 g; SODIUM FLUORIDE 0.22 g/100 g; AMINOCAPROIC ACID 0.05 g/100 g; GLYCYRRHIZINATE DIPOTASSIUM 0.04 g/100 g; URSODIOL 0.02 g/100 g; Curcuma xanthorrhiza oil 0.025 g/100 g; SEA SALT  3 g/100 g
INACTIVE INGREDIENTS: SORBITOL; Polyethylene Glycol 300; XANTHAN GUM; Poloxamer 407; Sodium Lauryl Sulfate; Sodium Bisulfite; Titanium Dioxide; WATER; Peppermint; FD&C BLUE NO. 1; D&C YELLOW NO. 10; METHYLPARABEN; SACCHARIN SODIUM

Drug Facts

DOSAGE AND ADMINISTRATION

Direction: Suggested brushing your teeth with proper amount for at least two times per day or following dentist / doctor's instruction.

Children between two to six should use about two to six should use about a size of a pea and should be supervised by adults while using.

WARNINGS

This product is for brushing teeth only and uneatable. If a rash occurs, stop using this product and consult a doctor or dentist.

If it comes in contact with eyes, cleanse off immediately and consult a doctor.

ACTIVE INGREDIENT

SILICON DIOXIDE 20%

Sodium Fluoride 0.22%

AMINOCAPROIC ACID 0.05%

GLYCYRRHIZINATE DIPOTASSIUM 0.04%

URSODIOL 0.02 %

Curcuma xanthorrhiza oil 0.025%

SEA SALT 3.0%

INACTIVE INGREDIENT

SORBITOL, Polyethylene Glycol 300, Xanthan Gum, Carboxymethylcellulose, Sodium Saccharin, METHYLPARABEN, Poloxamer 407, Sodium Lauryl Sulfate, Sodium Bisulfite, Titanium Dioxide, FD C Blue No.1, D C YELLOW NO. 10, Peppermint, water.

DOSAGE AND ADMINISTRATION

Suggest brushing your teeth with proper amount for at least two times per day or following dentist/doctor's instruction.

Children between two to six should use about a size of a pea and should be supervised by adults while using.

INDICATIONS AND USAGE

Life long gum care.

PACKAGE LABEL

Bamboo salt toothpaste

KEEP OUT OF REACH OF CHILDREN

Store this product away from children and supervise them while using.

PURPOSE

use to care gum.